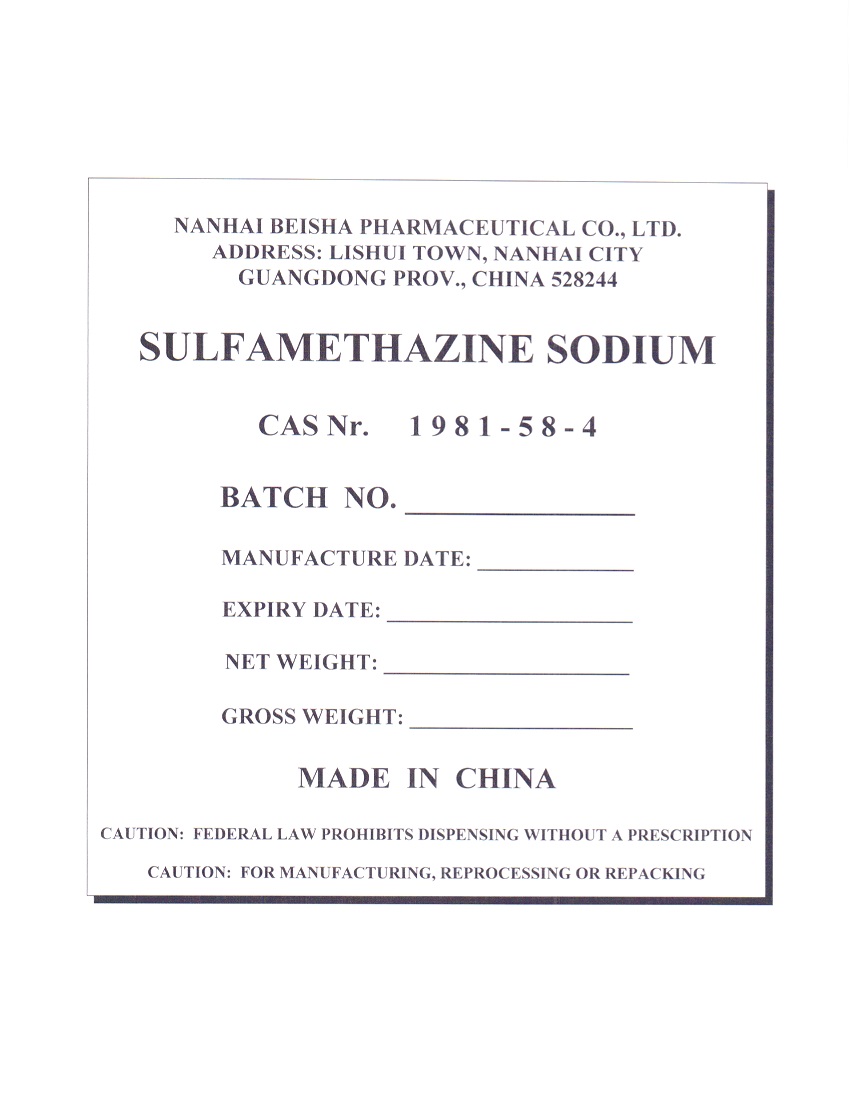 DRUG LABEL: SULFAMETHAZINE SODIUM
NDC: 63422-702 | Form: POWDER
Manufacturer: NANHAI BEISHA PHARMACEUTICAL CO., LTD.
Category: other | Type: BULK INGREDIENT - ANIMAL DRUG
Date: 20250806

ACTIVE INGREDIENTS: SULFAMETHAZINE SODIUM 25 kg/25 kg

PACKAGE LABEL

Add image transcription here...

Add image transcription here...